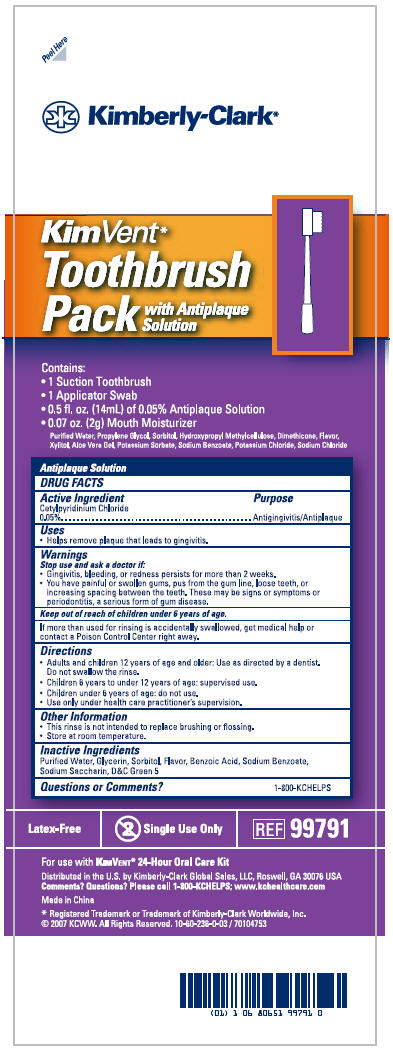 DRUG LABEL: Kimvent Oral  Care Toothbrush  pack
NDC: 69697-980 | Form: KIT | Route: ORAL
Manufacturer: Halyard Health
Category: otc | Type: HUMAN OTC DRUG LABEL
Date: 20150323

ACTIVE INGREDIENTS: Cetylpyridinium Chloride 0.0005 mg/1 mL
INACTIVE INGREDIENTS: Water; Benzoic Acid; Saccharin Sodium; Sodium Benzoate; Glycerin; D&C Green No. 5; Sorbitol; Mint

KimVent* Toothbrush Pack
with Antiplaque Solution

Drug Facts

Active Ingredient

Cetylpyridinium Chloride 0.05

Purpose

Antigingivitis/Antiplaque

Uses

- Helps remove plaque that leads to gingivitis.

Warnings

Stop use and ask a doctor if:

- Gingivitis, bleeding, or redness persists for more than 2 weeks.
- You have painful or swollen gums, pus from the gum line, loose teeth, or increasing spacing between the teeth. These may be signs or symptoms or periodontitis, a serious form of gum disease.

Keep out of reach of children under 6 years of age.

If more than used for rinsing is accidentally swallowed, get medical help or contact a Poison Control Center right away.

Directions

- Adults and children 12 years of age and older: Use as directed by a dentist. Do not swallow the rinse.
- Children 6 years to under 12 years of age: supervised use.
- Children under 6 years of age: do not use.
- Use only under health care practitioner's supervision.

Other Information

- This rinse is not intended to replace brushing or flossing.
- Store at room temperature.

Inactive Ingredients

Purified Water, Glycerin, Sorbitol, Flavor, Benzoic Acid, Sodium Benzoate, Sodium Saccharin, D&C Green 5

Questions or Comments?

1-800-KCHELPS

Distributed in the U.S. by Kimberly-Clark Global Sales, LLC, Roswell, GA 30076 USA

PRINCIPAL DISPLAY PANEL - Kit Carton

Peel Here

Kimberly-Clark*

Kim Vent*
Toothbrush
Pack with Antiplaque
Solution

Contains:

- 1 Suction Toothbrush
- 1 Applicator Swab
- 0.5 fl. oz. (14mL) of 0.05% Antiplaque Solution
- 0.07 oz. (2g) Mouth Moisturizer
  Purified Water, Propylene Glycol Sorbitol, Hydroxypropyl Methylcellulose, Dimethicone, Flavor,
  Xylitol, Aloe Vera Gel, Potassium Sorbate, Sodium Benzoate, Potassium Chloride, Sodium Chloride